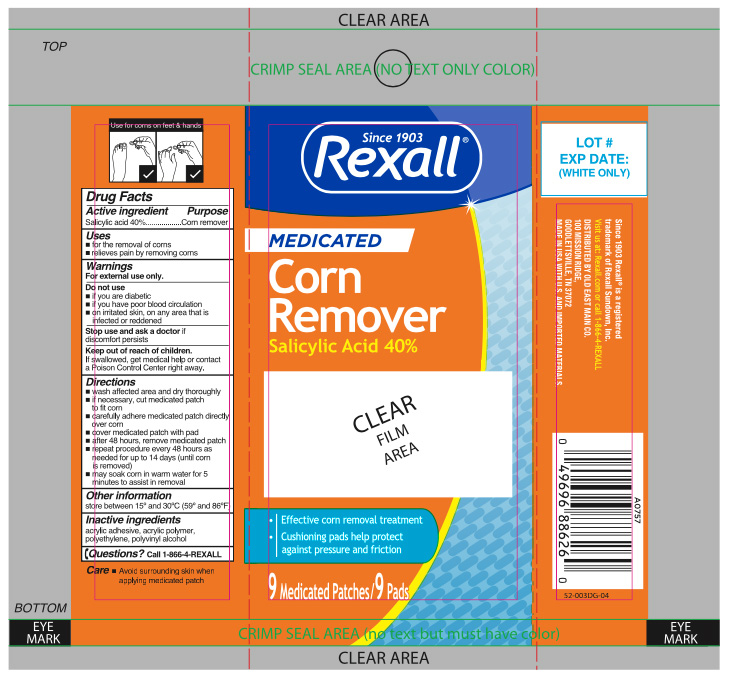 DRUG LABEL: Medicated Corn Remover
NDC: 55910-857 | Form: PATCH
Manufacturer: Dolgencorp, Inc. (Dollar General & Rexall)
Category: otc | Type: HUMAN OTC DRUG LABEL
Date: 20251230

ACTIVE INGREDIENTS: SALICYLIC ACID 40 mg/9 1
INACTIVE INGREDIENTS: POLYVINYL ALCOHOL; HIGH DENSITY POLYETHYLENE

Rexall Medicated Corn Removers

Active ingredient

Salicylic acid 40%

Purpose

Corn remover

Uses

- for the removal of corns
- relieves pain by removing corns

Warnings

For external use only.

Do not use

- if you are diabetic
- if you have poor blood circulation
- on irritated skin, on any area that is infected or reddened

Stop Use and Ask a doctor

if discomfort persists

Keep out of reach of children.

If swallowed, get medical help or contact a Poison Control Center right away.

Directions

- wash affected area and dry thoroughly
- if necessary, cut medicated patch to fit corn
- carefully adhere medicated patch directly over corn
- cover medicated patch with pad
- after 48 hours, remove medicated patch
- repeat procedure every 48 hours as needed for up to 14 days (until corn is removed)
- may soak corn in warm water for 5 minutes to assist in removal

Other information

store between 15° to 30°C (59° and 86°F)

Inactive ingredients

acrylic adhesive, acrylic polymer, polyethylene, polyvinyl alcohol

Questions?

call 1-866-4-REXALL

Principal Display Panel

Rexall Pharmacy

MEDICATED

CORN REMOVERS
Salicylic Acid 40%

Effective corn removal treartment

Cushioning pads help protect against pressure & friction

9 MEDICATED PATCHES/ 9 Pads